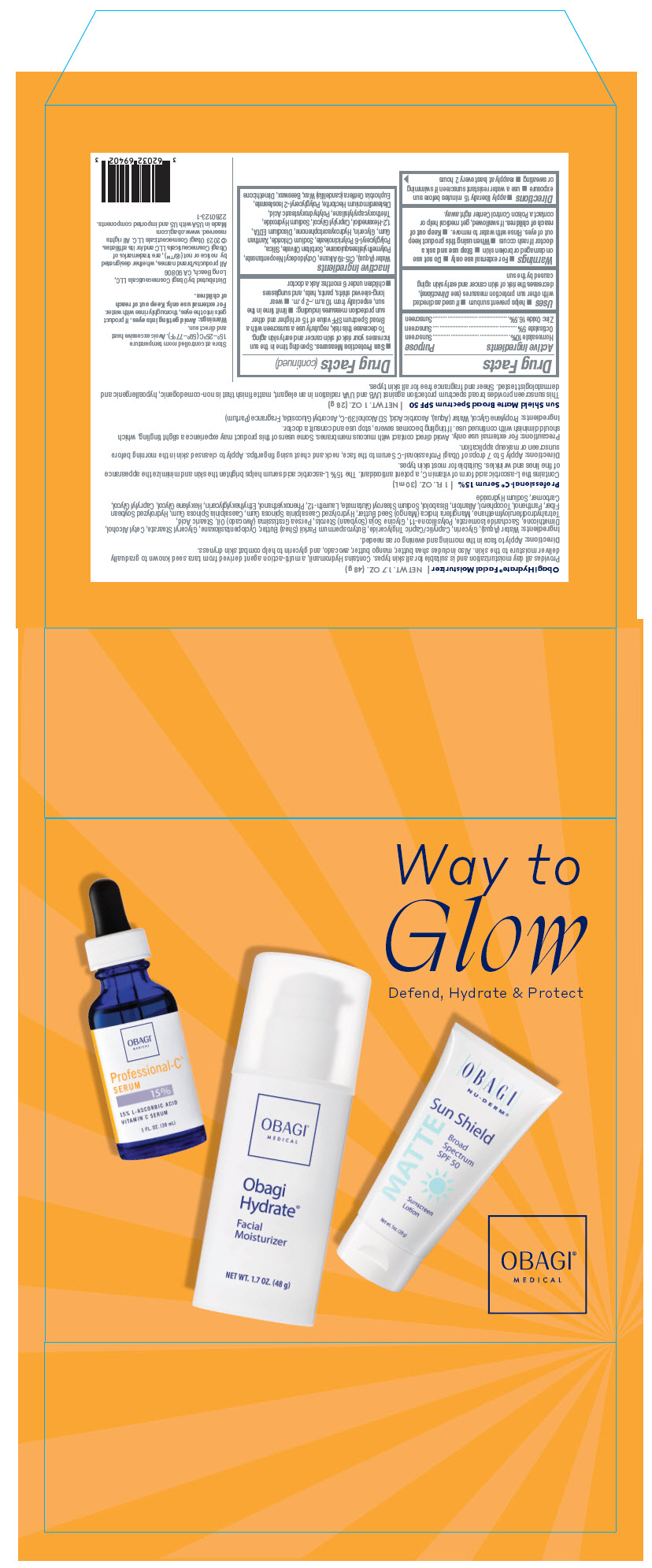 DRUG LABEL: Obagi Medical Way to Glow Kit
NDC: 62032-690 | Form: KIT | Route: TOPICAL
Manufacturer: Obagi Cosmeceuticals LLC
Category: otc | Type: HUMAN OTC DRUG LABEL
Date: 20250320

ACTIVE INGREDIENTS: OCTISALATE 50 mg/1 g; HOMOSALATE 100 mg/1 g; ZINC OXIDE 165 mg/1 g
INACTIVE INGREDIENTS: POLYGLYCERYL-2 ISOSTEARATE; POLYMETHYLSILSESQUIOXANE (4.5 MICRONS); 1,2-HEXANEDIOL; CAPRYLYL GLYCOL; DISTEARDIMONIUM HECTORITE; EDETATE DISODIUM ANHYDROUS; SODIUM CHLORIDE; C15-19 ALKANE; DIMETHICONE; GLYCERIN; POLYGLYCERYL-6 POLYRICINOLEATE; POLYHYDROXYSTEARIC ACID (2300 MW); SILICON DIOXIDE; SODIUM HYDROXIDE; YELLOW WAX; HYDROXYACETOPHENONE; OCTYLDODECYL NEOPENTANOATE; CANDELILLA WAX; SORBITAN OLIVATE; TRIETHOXYCAPRYLYLSILANE; WATER; XANTHAN GUM

Obagi Medical Way to Glow Kit

Drug Facts

Active ingredients | Purpose
Homosalate 10% | Sunscreen
Octisalate 5% | Sunscreen
Zinc Oxide 16.5% | Sunscreen

PURPOSE

Sunscreen

Uses

- helps prevent sunburn
- if used as directed with other sun protection measures (see Directions), decreases the risk of skin cancer and early skin aging caused by the sun

Warnings

- For external use only
- Do not use on damaged or broken skin
- Stop use and ask a doctor if rash occurs
- When using this product keep out of eyes. Rinse with water to remove.

- Keep out of reach of children. If swallowed, get medical help or contact a Poison Control Center right away.

Directions

- apply liberally 15 minutes before sun exposure
- use a water resistant sunscreen if swimming or sweating
- reapply at least every 2 hours
- Sun Protection Measures. Spending time in the sun increases your risk of skin cancer and early skin aging. To decrease this risk, regularly use a sunscreen with a Broad Spectrum SPF value of 15 or higher and other sun protection measures including:
  - limit time in the sun, especially from 10 a.m.–2 p.m.
  - wear long-sleeved shirts, pants, hats, and sunglasses
  - children under 6 months: Ask a doctor

Inactive Ingredients

Water (Aqua), C15-19 Alkane, Octyldodecyl Neopentanoate, Polymethylsilsesquioxane, Sorbitan Olivate, Silica, Polyglyceryl-6 Polyricinoleate, Sodium Chloride, Xanthan Gum, Glycerin, Hydroxyacetophenone, Disodium EDTA, 1,2-Hexanediol, Caprylyl Glycol, Sodium Hydroxide, Triethoxycaprylylsilane, Polyhydroxystearic Acid, Disteardimonium Hectorite, Polyglyceryl-2 Isostearate, Euphorbia Cerifera (candelilla) Wax, Beeswax, Dimethicone

Distributed by Obagi Cosmeceuticals LLC,
Long Beach, CA 90806

PRINCIPAL DISPLAY PANEL - Kit Carton

Way to
Glow
Defend, Hydrate & Protect

OBAGI®
MEDICAL